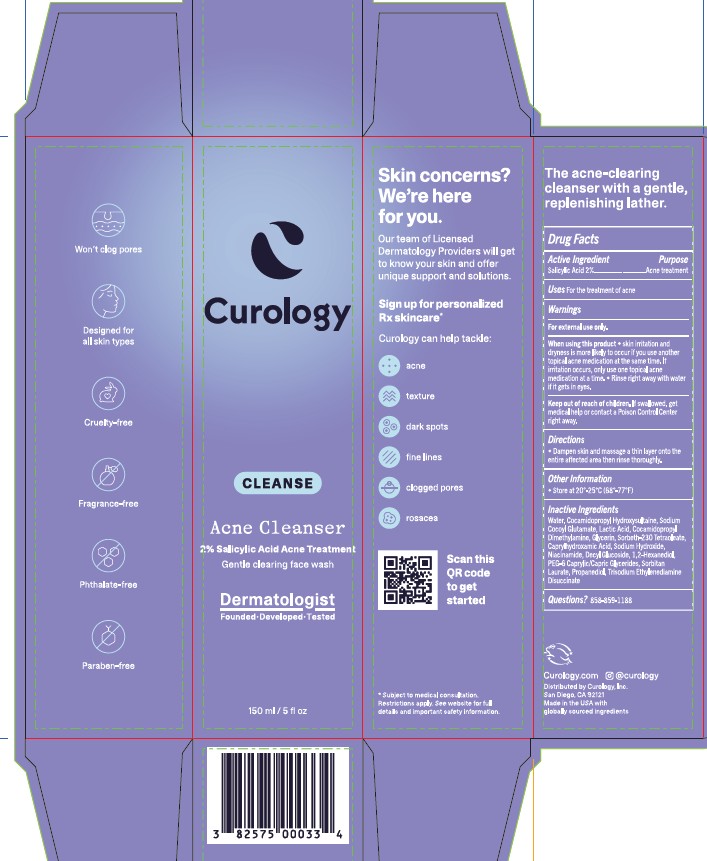 DRUG LABEL: Acne Cleanser
NDC: 82575-510 | Form: LIQUID
Manufacturer: Curology
Category: otc | Type: HUMAN OTC DRUG LABEL
Date: 20251125

ACTIVE INGREDIENTS: SALICYLIC ACID 2 g/100 g
INACTIVE INGREDIENTS: SORBITAN LAURATE; SODIUM HYDROXIDE; LACTIC ACID; WATER; COCAMIDOPROPYL DIMETHYLAMINE; TRISODIUM ETHYLENEDIAMINE DISUCCINATE; 1,2-HEXANEDIOL; COCAMIDOPROPYL HYDROXYSULTAINE; GLYCERIN; SORBETH-40 TETRAOLEATE; NIACINAMIDE; DECYL GLUCOSIDE; PROPANEDIOL; CAPRYLHYDROXAMIC ACID; PEG-6 CAPRYLIC/CAPRIC GLYCERIDES; SODIUM COCOYL GLUTAMATE

Curology Salicylic Acid Facial Cleanser

Drug Facts

Active Ingredient

Active Ingredient | Purpose
Salicylic Acid 2% | Acne Treatment

Uses

For the treatment of acne

WARNINGS

For external use only

When using this product

- Skin irritation and dryness is more likely to occur if you use another topical acne medication at the same time. If irritation occurs, only use one topical acne medication at a time.
- Rinse right away with water if it gets in eyes.

Keep out of reach of children. If swallowed, get medical help or contact a Poison Control Center right away.

Directions

- Dampen skin and massage a thin layer onto the entire affected area then rinse thoroughly.

Other Information

- Store at 20o-25oC (68o-77oF)

INACTIVE INGREDIENT

Water, Cocamidopropyl Hydroxysultaine, Sodium Cocoyl Glutamate, Lactic Acid, Cocamidopropyl Dimethylamine, Glycerin, Sorbeth-230 Tetraoleate, Caprylhydroxamic Acid, Sodium Hydroxide, Niacinamide, Decyl Glucoside, 1,2-Hexanediol, PEG-6 Caprylic/Capric Glycerides, Sorbitan Laurate, Propanediol, Trisodium Ethylenediamine Disuccinate

Questions?

858-859-1188

Curology Salicylic Acne Cleanser - 150 mL Carton

Curology

CLEANSE

Acne Cleanser

2% Salicylic Acid Acne Treatment

Gentle clearing face wash

Dermatologist

Founded | Developed | Tested